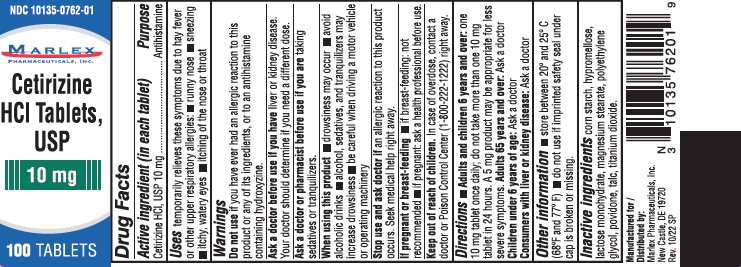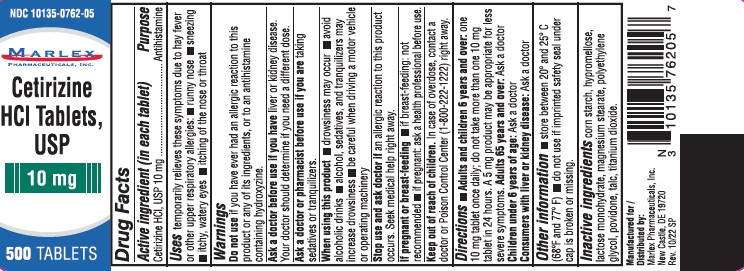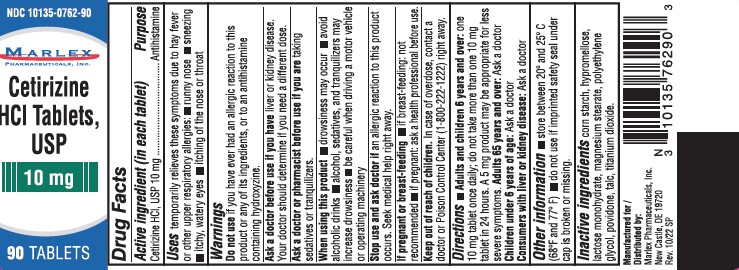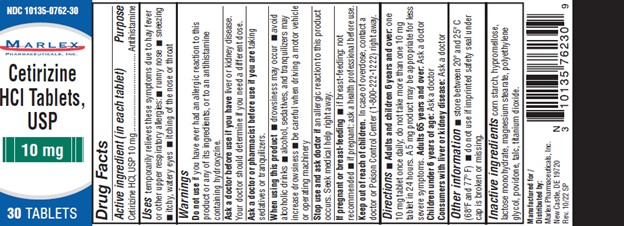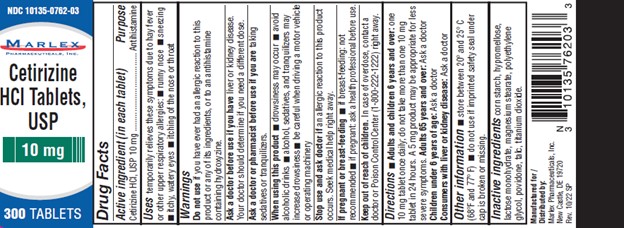 DRUG LABEL: Cetirizine Hydrochloride
NDC: 10135-762 | Form: TABLET
Manufacturer: Marlex Pharmaceuticals, Inc
Category: otc | Type: HUMAN OTC DRUG LABEL
Date: 20250923

ACTIVE INGREDIENTS: CETIRIZINE HYDROCHLORIDE 10 mg/1 1
INACTIVE INGREDIENTS: POVIDONE, UNSPECIFIED; LACTOSE MONOHYDRATE; MAGNESIUM STEARATE; STARCH, CORN; TALC; TITANIUM DIOXIDE; HYPROMELLOSE, UNSPECIFIED; POLYETHYLENE GLYCOL, UNSPECIFIED

Cetirizine Hydrochloride

Drug Facts

Active ingredient (in each tablet)

Cetirizine HCl, USP 10 mg

Purpose

Antihistamine

Uses

temporarily relieves these symptoms due to hay fever or other upper respiratory allergies:

- runny nose
- sneezing
- itchy, watery eyes
- itching of the nose or throat

Warnings

.

DO NOT USE

Do not useif you have ever had an allergic reaction to this product or any of its ingredients or to an antihistamine containing hydroxyzine.

Ask a doctor before use if you have liver or kidney disease. Your doctor should determine if you need a different dose.

Ask a doctor or pharmacist before use if you are taking sedatives or tranquilizers.

When using this product

- drowsiness may occur
- avoid alcoholic drinks
- alcohol, sedatives, and tranquilizers may increase drowsiness
- be careful when driving a motor vehicle or operating machinery

Stop use and ask a doctor if an allergic reaction to this product occurs. Seek medical help right away.

If pregnant or breast-feeding

- if breast-feeding: not recommended
- if pregnant: ask a health professional before use.

Keep out of reach of children.In case of overdose, contact a doctor or Poison Control Center (1-800-222-1222) right away.

Directions

adults and children 6 years and over | one 10 mg tablet once daily; do not take more than one 10 mg tablet in 24 hours. A 5 mg product may be appropriate for less severe symptoms.
adults 65 years and over | ask a doctor
children under 6 years of age | ask a doctor
consumers with liver or kidney disease | ask a doctor

Other information

- store between 20° and 25° C (68° and 77° F)
- do not use if imprinted safety seal under cap is broken or missing.

Inactive ingredients

corn starch, hypromellose, lactose monohydrate, magnesium stearate, polyethylene glycol, povidone, talc, titanium dioxide

Manufactured for/ Distributed by:

Marlex Pharmaceuticals, Inc.

New Castle, DE 19720

Rev. 10/22 SP

PRINCIPAL DISPLAY PANEL - 10 mg Tablet Bottle Label

NDC 10135-0762-30

Allergy Relief
Cetirizine HCl Tablets, USP 10 mg
ANTIHISTAMINE

30 TABLETS

PRINCIPAL DISPLAY PANEL - 10 mg Tablet Bottle Label

NDC 10135-0762-90

Allergy Relief
Cetirizine HCl Tablets, USP 10 mg
ANTIHISTAMINE

90 TABLETS

PRINCIPAL DISPLAY PANEL - 10 mg Tablet Bottle Label

NDC 10135-0762-01

Allergy Relief
Cetirizine HCl Tablets, USP 10 mg
ANTIHISTAMINE

100 TABLETS

PRINCIPAL DISPLAY PANEL - 10 mg Tablet Bottle Label

NDC 10135-0762-03

Allergy Relief
Cetirizine HCl Tablets, USP 10 mg
ANTIHISTAMINE

300 TABLETS

PRINCIPAL DISPLAY PANEL - 10 mg Tablet Bottle Label

NDC 10135-0762-05

Allergy Relief
Cetirizine HCl Tablets, USP 10 mg
ANTIHISTAMINE

500 TABLETS